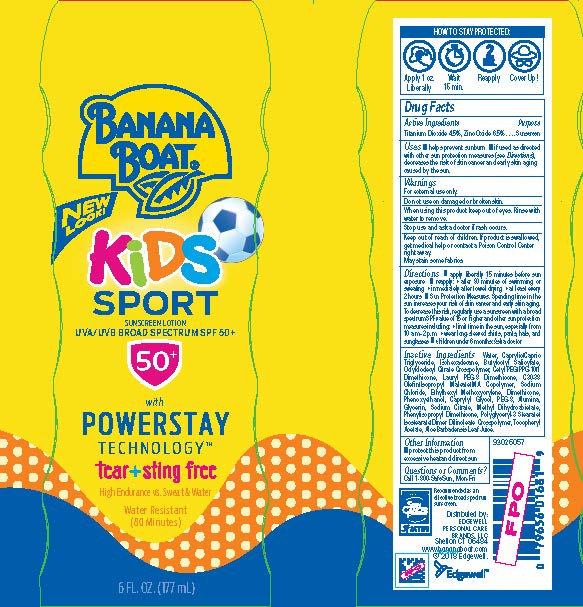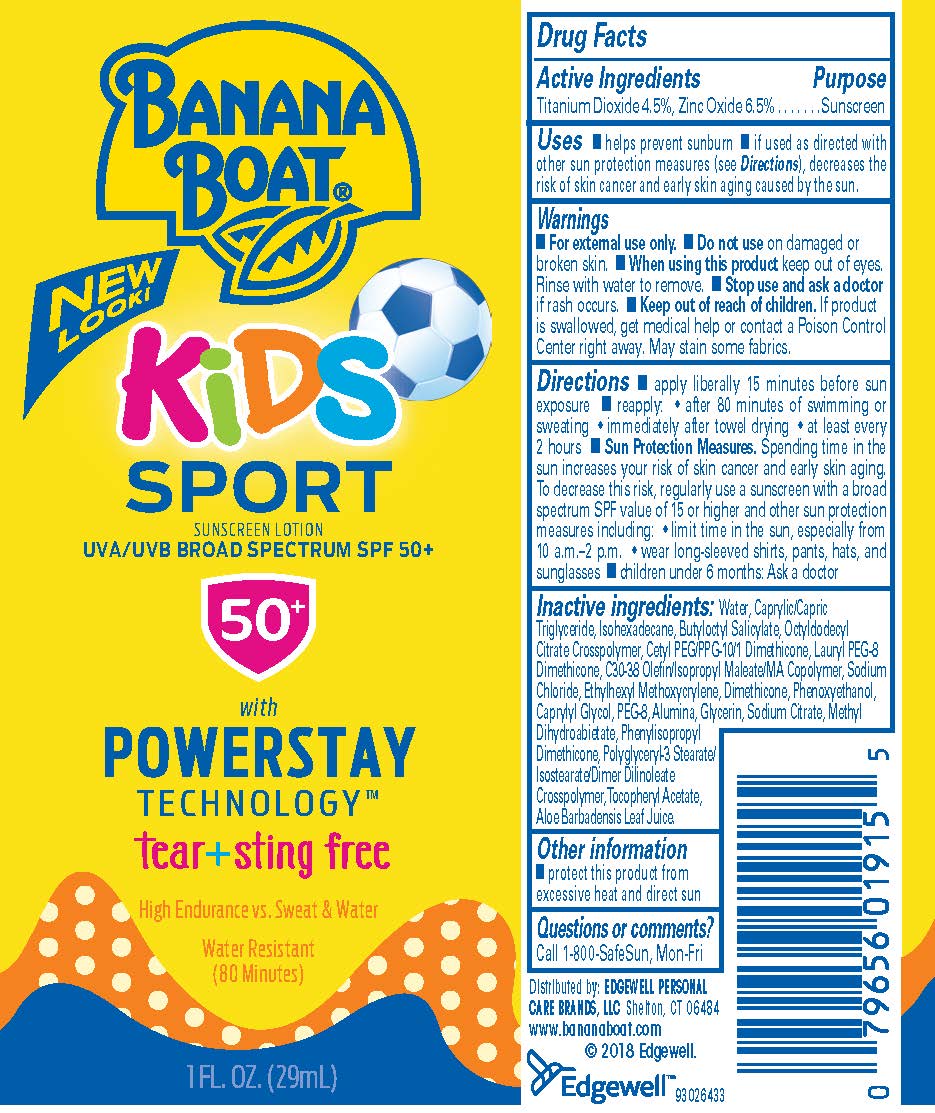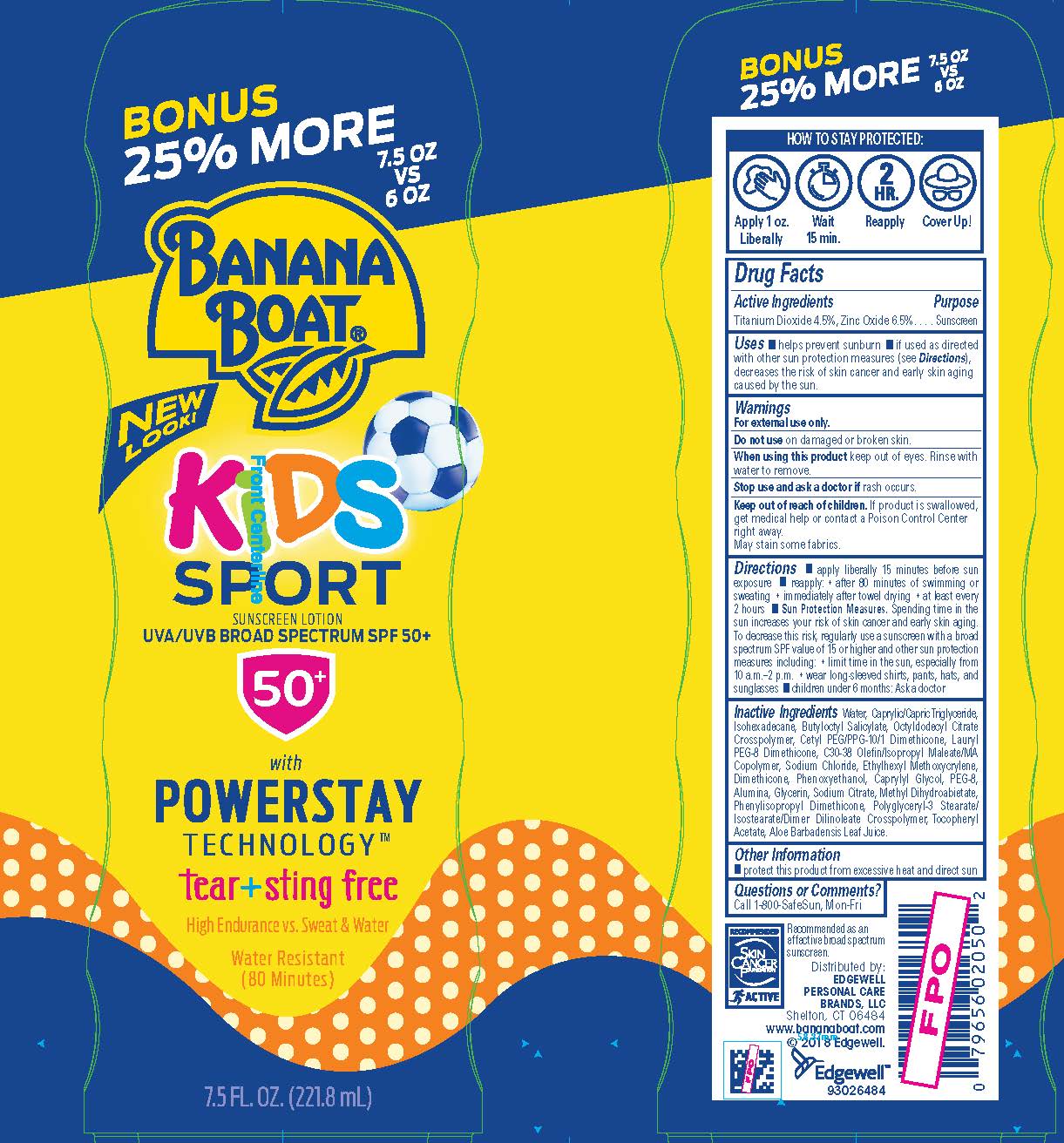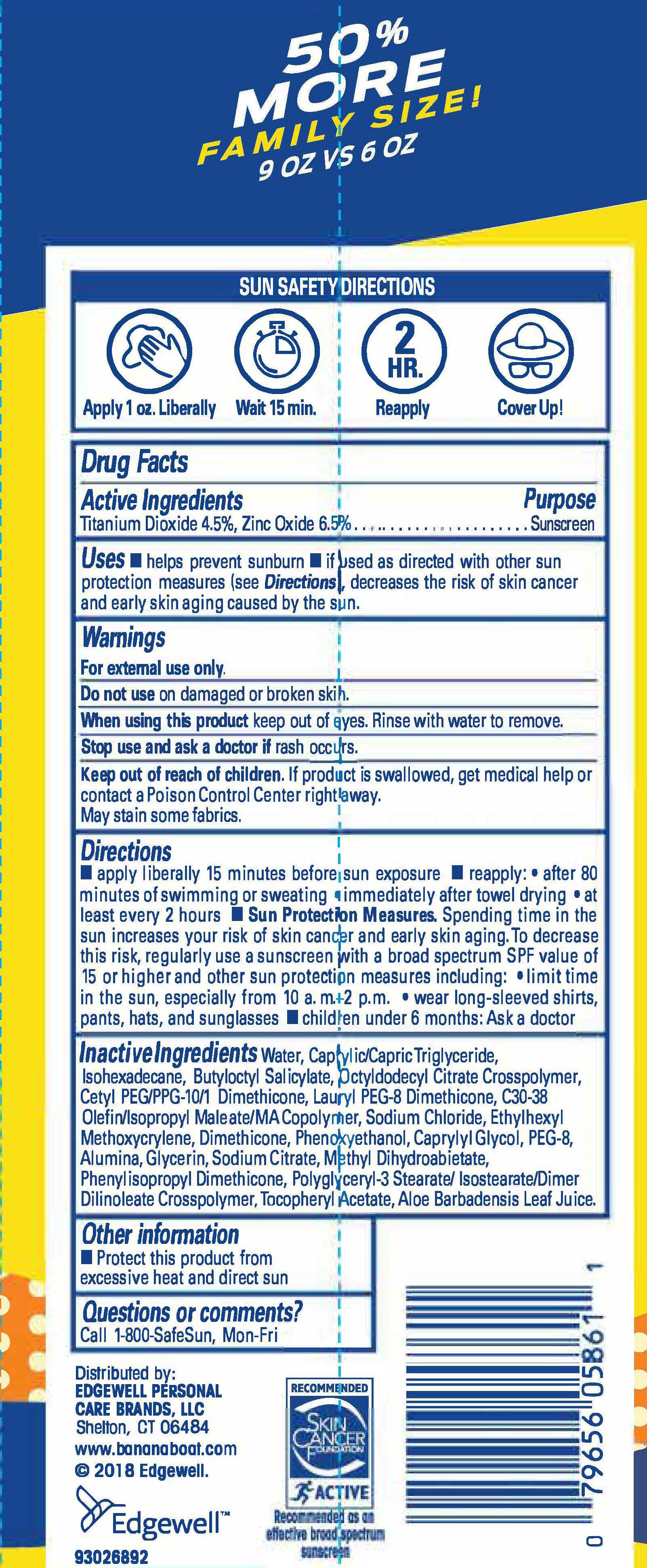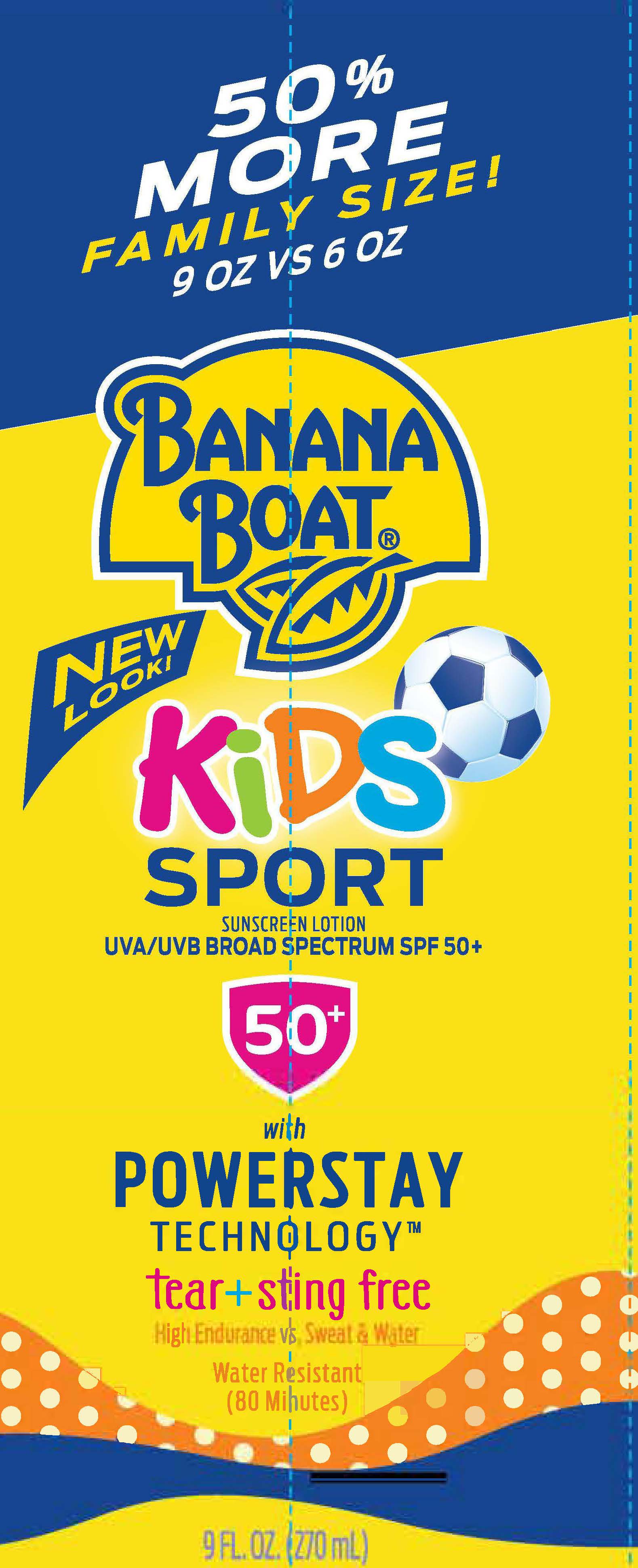 DRUG LABEL: Banana Boat
NDC: 63354-755 | Form: LOTION
Manufacturer: Edgewell Personal Care Brands, LLC
Category: otc | Type: HUMAN OTC DRUG LABEL
Date: 20241023

ACTIVE INGREDIENTS: TITANIUM DIOXIDE 4.5 g/100 g; ZINC OXIDE 6.5 g/100 g
INACTIVE INGREDIENTS: ISOHEXADECANE; SODIUM CHLORIDE; DIMETHICONE; PHENOXYETHANOL; CAPRYLYL GLYCOL; ALUMINUM OXIDE; SODIUM CITRATE; WATER; CETYL PEG/PPG-10/1 DIMETHICONE (HLB 2); ETHYLHEXYL METHOXYCRYLENE; GLYCERIN; METHYL DIHYDROABIETATE; ALOE VERA LEAF; BUTYLOCTYL SALICYLATE; .ALPHA.-TOCOPHEROL ACETATE, DL-

Active Ingredients

Titanium Dioxide 4.5%, Zinc Oxide 6.5%

Purpose

Sunscreen

Uses

- helps prevent sunburn
- if used as directed with other sun protection measures (see Directions), decreases the risk of skin cancer and early skin aging caused by the sun.

Warnings

For external use only

Do not use

on damaged or broken skin

When using this product

keep out of eyes. Rinse with water to remove.

Stop use and ask a doctor

if rash occurs

Keep out of reach of children

If product is swallowed, get medical help or contact a Poison Control Center right away.

May stain some fabrics.

Directions

- Apply liberally 15 minutes before sun exposure
- Reapply: • after 80 minutes of swimming or sweating • immediately after towel drying • at least every 2 hours
- Sun Protection Measures. Spending time in the sun increases your risk of skin cancer and early skin aging. To decrease this risk, regularly use a sunscreen with a broad spectrum SPF of 15 or higher and other sun protection measures including: • limit time in the sun, especially from 10 a.m.–2 p.m. • wear long-sleeved shirts, pants, hats, and sunglasses
- Children under 6 months: Ask a doctor

Inactive ingredients

Water, Caprylic/Capric Triglyceride, Isohexadecane, Butyloctyl Salicylate, Octyldodecyl Citrate Crosspolymer, Cetyl PEG/PPG-10/1 Dimethicone, Lauryl PEG-8 Dimethicone, C30-38 Olefin/Isopropyl Maleate/MA Copolymer, Sodium Chloride, Ethylhexyl Methoxycrylene, Dimethicone,Phenoxyethanol, Caprylyl Glycol, PEG-8, Alumina,Glycerin, Sodium Citrate, Methyl Dihydroabietate,Phenylisopropyl Dimethicone, Polyglyceryl-3 Stearate/Isostearate/Dimer Dilinoleate Crosspolymer, Tocopheryl Acetate, Aloe Barbadensis Leaf Juice.

Other Information

Protect this product from excessive heat and direct sun

Questions or Comments?

Call 1-800-SafeSun, Mon-Fri

Principal Display Panel

BANANA
BOAT
NEW
LOOK!
KiDS
SPORT
SUNSCREEN LOTION
UVA/UVB BROAD SPRECTRUM SPF 50+
50+
with
POWERSTAY
TECHNOLOGY
tear+sting free
High Endurance vs. Sweat & Water
Water Resistant
(80 Minutes)
1 FL.OZ. (29 mL)

BANANA
BOAT
NEW
LOOK!
KiDS
SPORT
SUNSCREEN LOTION
UVA/UVB BROAD SPRECTRUM SPF 50+
50+
with
POWERSTAY
TECHNOLOGY
tear+sting free
High Endurance vs. Sweat & Water
Water Resistant
(80 Minutes)
6 FL.OZ. (177 mL)

BONUS
25% MORE
7.5 oz vs 6 oz
BANANA
BOAT
NEW
LOOK!
KiDS
SPORT
SUNSCREEN LOTION
UVA/UVB BROAD SPRECTRUM SPF 50+
50+
with
POWERSTAY
TECHNOLOGY
tear+sting free
High Endurance vs. Sweat & Water
Water Resistant
(80 Minutes)
7.5 FL.OZ. (221.8 mL)

50%
MORE
FAMILY SIZE!
9 OZ VS 6 OZ
BANANA
BOAT
NEW
LOOK!
KiDS
SPORT
SUNSCREEN LOTION
UVA/UVB BROAD SPRECTRUM SPF 50+
50+
with
POWERSTAY
TECHNOLOGY
tear+sting free
High Endurance vs. Sweat & Water
Water Resistant
(80 Minutes)
9 FL.OZ. (270 mL)